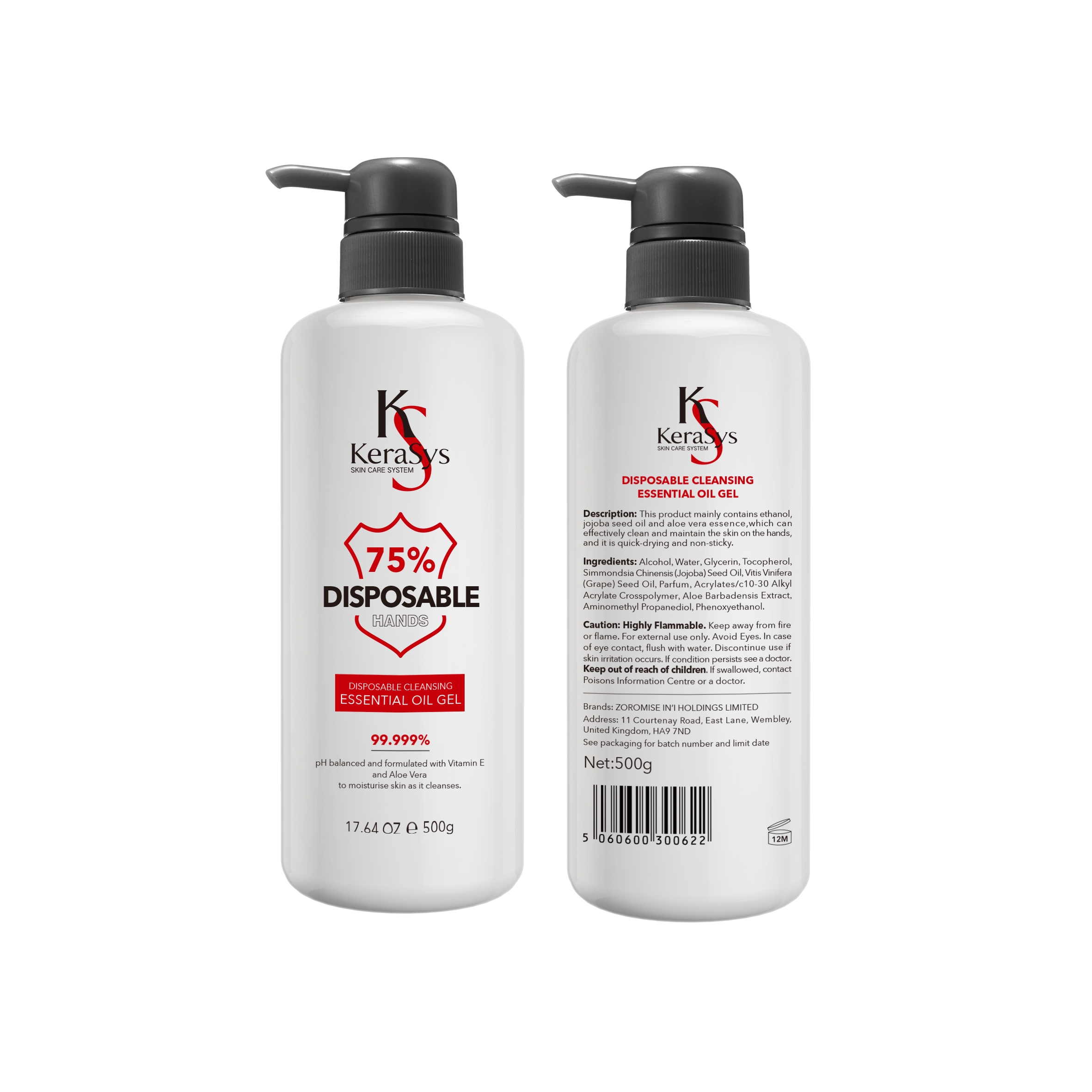 DRUG LABEL: DISPOSABLE HAND SANITISER
NDC: 77332-001 | Form: GEL
Manufacturer: Guangzhou Taimei Trading Co., Ltd.
Category: otc | Type: HUMAN OTC DRUG LABEL
Date: 20200507

ACTIVE INGREDIENTS: ALCOHOL 75 mL/100 g
INACTIVE INGREDIENTS: ALPHA-TOCOPHEROL ACETATE; GLYCERIN; ALOE VERA LEAF; WATER; AMINOMETHYL PROPANEDIOL; CARBOMER INTERPOLYMER TYPE A (ALLYL SUCROSE CROSSLINKED)

DISPOSABLE HAND SANITISER

Active Ingredient(s)

Alcohol 75% v/v. Purpose: Antiseptic

Purpose

Antiseptic, Hand Sanitizer

Use

This product mainly contains ethanolm jojoba seed oil and aloe vera essence, which can effectively clean and maintain the skin on the hands, and it is quick-drying and non-sticky.

Warnings

Highly flammable. Keep away from fire or flame. For external use only.

WHEN USING

Avoid eyes. In case of eye contact, flush with water

STOP USE

Discontinue use if skin irritation occurs. If condition persists see a doctor.

Keep out of reach of children. If swallowed, contact Poison Control Center or a doctor.

Directions

Place enough product on hands to cover all surfaces. Rub hands together until dry.

Other information

Store between 15-30C (59-86F)

Inactive ingredients

Aloe barbadensis leaf juice, Glycerin, Tocopheryl acetate, Parfum, Acrylate/C10-30 alkyl acrylate crosspolymer, Amino-methyl-propanediol, water

Package Label - Principal Display Panel

500g NDC: 77332-001-01